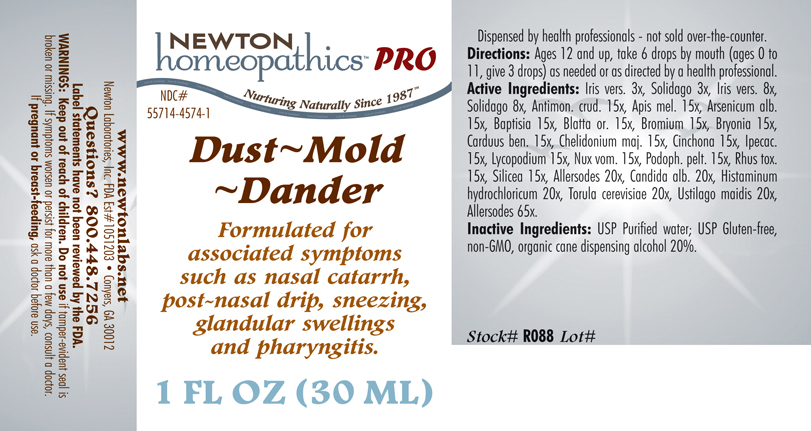 DRUG LABEL: Dust - Mold - Dander 
NDC: 55714-4574 | Form: LIQUID
Manufacturer: Newton Laboratories, Inc.
Category: homeopathic | Type: HUMAN PRESCRIPTION DRUG LABEL
Date: 20110601

ACTIVE INGREDIENTS: Felis Catus Skin 65 [hp_X]/1 mL; Canis Lupus Familiaris Skin 65 [hp_X]/1 mL; Oryctolagus Cuniculus Skin 65 [hp_X]/1 mL; Equus Caballus Skin 65 [hp_X]/1 mL; Serinus Canaria Feather 65 [hp_X]/1 mL; Gallus Gallus Feather 65 [hp_X]/1 mL; Anas Platyrhynchos Feather 65 [hp_X]/1 mL; Anser Anser Feather 65 [hp_X]/1 mL; Melopsittacus Undulatus Feather 65 [hp_X]/1 mL; Phasianus Colchicus Feather 65 [hp_X]/1 mL; Meleagris Gallopavo Feather 65 [hp_X]/1 mL; Felis Catus Hair 65 [hp_X]/1 mL; Human Dander 65 [hp_X]/1 mL; Canis Lupus Familiaris Hair 65 [hp_X]/1 mL; Equus Caballus Hair 65 [hp_X]/1 mL; Oryctolagus Cuniculus Hair 65 [hp_X]/1 mL; Human Hair 65 [hp_X]/1 mL; Human Skin 65 [hp_X]/1 mL; Sheep Wool 65 [hp_X]/1 mL; Bos Taurus Hair 65 [hp_X]/1 mL; Capra Hircus Hair 65 [hp_X]/1 mL; Cavia Porcellus Hair 65 [hp_X]/1 mL; Mesocricetus Auratus Hair 65 [hp_X]/1 mL; Wheat Gluten 20 [hp_X]/1 mL; Aspergillus Niger Var. Niger 20 [hp_X]/1 mL; Cladosporium Herbarum 20 [hp_X]/1 mL; House Dust 20 [hp_X]/1 mL; Candida Albicans 20 [hp_X]/1 mL; Histamine Dihydrochloride 20 [hp_X]/1 mL; Saccharomyces Cerevisiae 20 [hp_X]/1 mL; Ustilago Maydis 20 [hp_X]/1 mL; Antimony Trisulfide 15 [hp_X]/1 mL; Apis Mellifera 15 [hp_X]/1 mL; Arsenic Trioxide 15 [hp_X]/1 mL; Baptisia Tinctoria Root 15 [hp_X]/1 mL; Blatta Orientalis 15 [hp_X]/1 mL; Bromine 15 [hp_X]/1 mL; Bryonia Alba Root 15 [hp_X]/1 mL; Centaurea Benedicta 15 [hp_X]/1 mL; Chelidonium Majus 15 [hp_X]/1 mL; Cinchona Officinalis Bark 15 [hp_X]/1 mL; Ipecac 15 [hp_X]/1 mL; Lycopodium Clavatum Spore 15 [hp_X]/1 mL; Strychnos Nux-vomica Seed 15 [hp_X]/1 mL; Podophyllum 15 [hp_X]/1 mL; Toxicodendron Pubescens Leaf 15 [hp_X]/1 mL; Silicon Dioxide 15 [hp_X]/1 mL; Iris Versicolor Root 8 [hp_X]/1 mL; Solidago Virgaurea Flowering Top 8 [hp_X]/1 mL
INACTIVE INGREDIENTS: Alcohol; Water

Dust - Mold - Dander

INDICATIONS & USAGE SECTION

Formulated for associated symptoms such as nasal catarrh, post-nasal drip, sneezing, glandular swellings and pharyngitis.

DOSAGE & ADMINISTRATION SECTION

Directions: Ages 12 and up, take 6 drops by mouth (ages 0 to 11, give 3 drops) as needed or as directed by a health professional.

OTC - ACTIVE INGREDIENT SECTION

Allersodes 65x, Allersodes 20x, Candida alb. 20x, Histaminum hydrochloricum 20x, Torula cerevisiae 20x, Ustilago maidis 20x, Antimon. crud. 15x, Apis mel. 15x, Arsenicum alb. 15x, Baptisia 15x, Blatta or. 15x, Bromium 15x, Bryonia 15x, Carduus ben. 15x, Chelidonium maj. 15x, Cinchona 15x, Ipecac. 15x, Lycopodium 15x, Nux vom. 15x, Podoph. pelt. 15x, Rhus tox. 15x, Silicea 15x, Iris versicolor 8x, Solidago 8x, Iris versicolor 3x, Solidago 3x.

OTC - PURPOSE SECTION

Formulated for associated symptoms such as nasal catarrh, post-nasal drip, sneezing, glandular swellings and pharyngitis.

INACTIVE INGREDIENT SECTION

USP Purified Water; USP Gluten-free, non-GMO, organic cane dispensing alcohol 20%.

QUESTIONS SECTION

www.newtonlabs.net Newton Laboratories, Inc. FDA Est # 1051203 - Conyers, GA 30012
Questions? 1.800.448.7256

WARNINGS SECTION

Warning: Keep our of reach of children. Do not use if tamper-evident seal is broken or missing. If symptoms worsen or persist for more than a few days, consult a doctor. If pregnant or breast-feeding, ask a doctor before use.

OTC - PREGNANCY OR BREAST FEEDING SECTION

If pregnant or breast-feeding, ask a doctor before use.

OTC - KEEP OUT OF REACH OF CHILDREN SECTION

Keep out of reach of children.